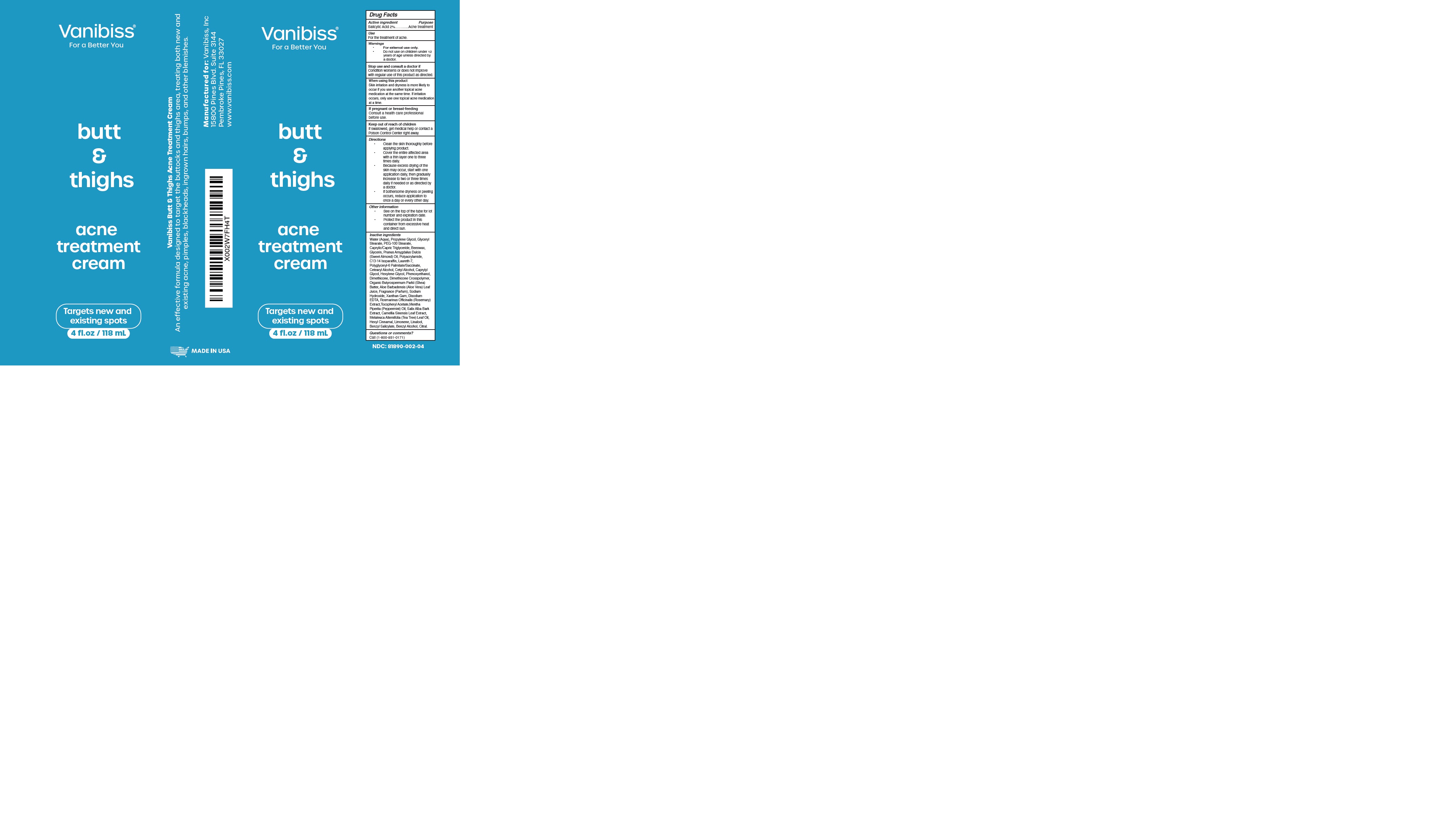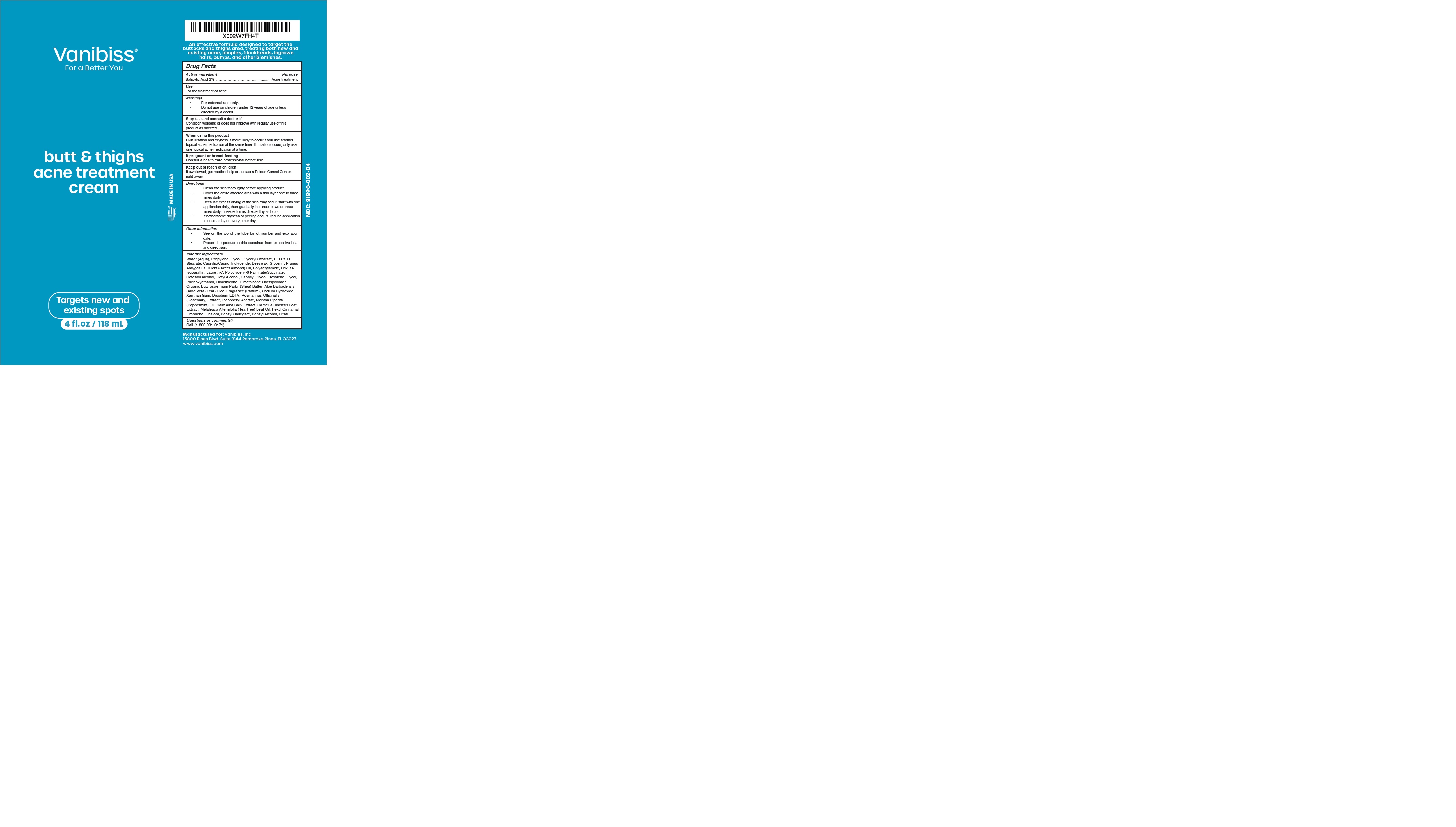 DRUG LABEL: VANIBISS BUTT AND THIGHS
NDC: 81890-002 | Form: CREAM
Manufacturer: Vanibiss Inc
Category: otc | Type: HUMAN OTC DRUG LABEL
Date: 20231003

ACTIVE INGREDIENTS: SALICYLIC ACID 2 g/100 mL
INACTIVE INGREDIENTS: GREEN TEA LEAF; WATER; POLYGLYCERIN-6; PHENOXYETHANOL; DIMETHICONE/DIENE DIMETHICONE CROSSPOLYMER; CETOSTEARYL ALCOHOL; ALMOND OIL; CETYL ALCOHOL; SHEA BUTTER; XANTHAN GUM; PROPYLENE GLYCOL; LAURETH-7; GLYCERIN; CAPRYLYL GLYCOL; EDETATE DISODIUM; .ALPHA.-TOCOPHEROL ACETATE; C13-14 ISOPARAFFIN; HEXYLENE GLYCOL; LIMONENE, (+)-; ALOE VERA LEAF; TEA TREE OIL; MEDIUM-CHAIN TRIGLYCERIDES; WHITE WAX; GLYCERYL STEARATE/PEG-100 STEARATE; SODIUM HYDROXIDE; ROSEMARY; PEPPERMINT OIL; .ALPHA.-HEXYLCINNAMALDEHYDE; LINALOOL, (+/-)-; BENZYL SALICYLATE; BENZYL ALCOHOL; CITRAL; SALIX ALBA BARK

81890-002-04

ACTIVE INGREDIENT

Salicylic Acid 2%

Purpose: Acne treatment

USE:

For the treatment of acne.

WARNINGS

For external use only.

Do not use on children under 12 years of age unless directed by a doctor.

Stop use and consult a doctor if

Condition worsens or does not improve with regular use of this product as directed.

WHEN USING

Skin irritation and dryness is more likely to occur if you use another topical acne medication at the same time. If irritation occurs, only use one topical acne medication at a time.

PREGNANCY OR BREAST FEEDING

If pregnant or breast-feeding, ask a health professional before use.

KEEP OUT OF REACH OF CHILDREN

If swallowed, get medical help or contact a Poison Control Center right away.

DIRECTIONS:

Clean the skin thoroughly before applying product.
Cover the entire affected area with a thin layer one to three times daily.
Because excess drying of the skin may occur, start with one application daily, then gradually increase to two or three times daily if needed or as directed by a doctor.

If bothersome dryness or peeling occurs, reduce application to once a day or every other day.

OTHER SAFETY INFORMATION

See on the top of the tube for lot number and expiration date.

Protect the product in this container from excessive heat and direct sun.

INACTIVE INGREDIENT

Water (Aqua), Propylene Glycol, Caprylic/Capric Triglyceride, Beeswax, Glycerin, Glyceryl Stearate, PEG-100 Stearate, Prunus Amygdalus Dulcis (Sweet Almond) Oil, Cetyl Alcohol, Organic Butyrospermum Parkii (Shea) Butter, Polyacrylamide, C13-14 Isoparaffin, Laureth-7, Caprylyl Glycol, Hexylene Glycol, Phenoxyethanol, Dimethicone, Dimethicone Crosspolymer, Polyglyceryl-6 Palmitate/Succinate, Cetearyl Alcohol, Aloe Barbadensis (Aloe Vera) Leaf Juice, Fragrance (Parfum), Sodium Hydroxide, Xanthan Gum, Disodium EDTA, Rosmarinus Officinalis (Rosemary) Extract, Tocopheryl Acetate, Mentha Piperita (Peppermint) Oil, Salix Alba Bark Extract, Camellia Sinensis Leaf Extract, Melaleuca Alternifolia (Tea Tree) Leaf Oil, Hexyl Cinnamal, D-Limonene, Linalool, Benzyl Salicylate, Benzyl Alcohol, Citral.

QUESTIONS

Call (1-800-931-0171)